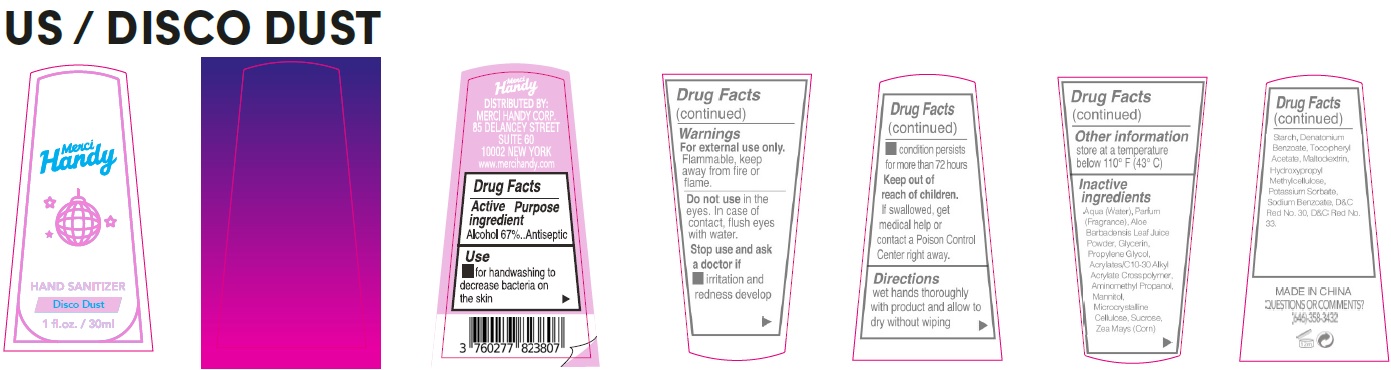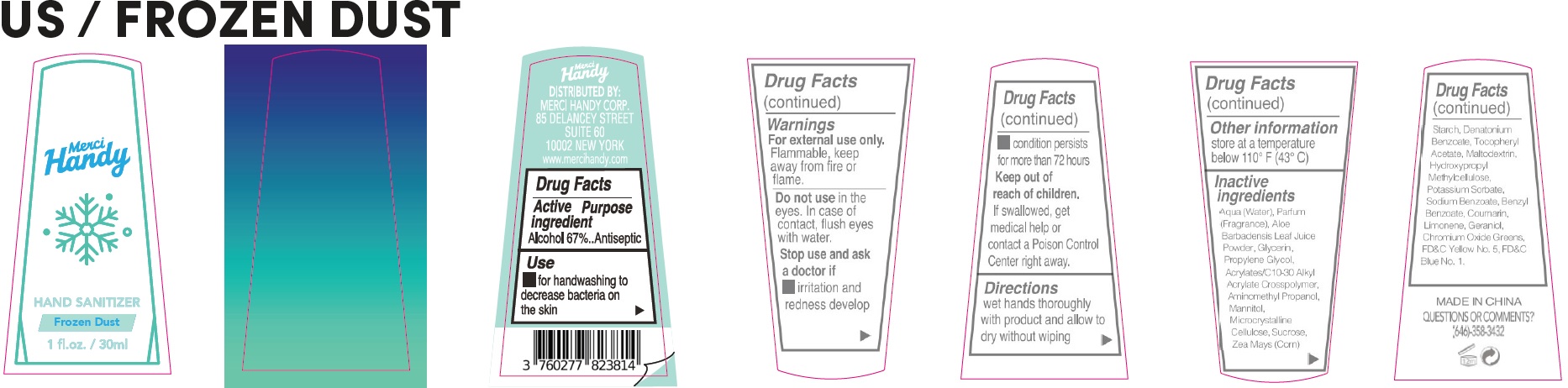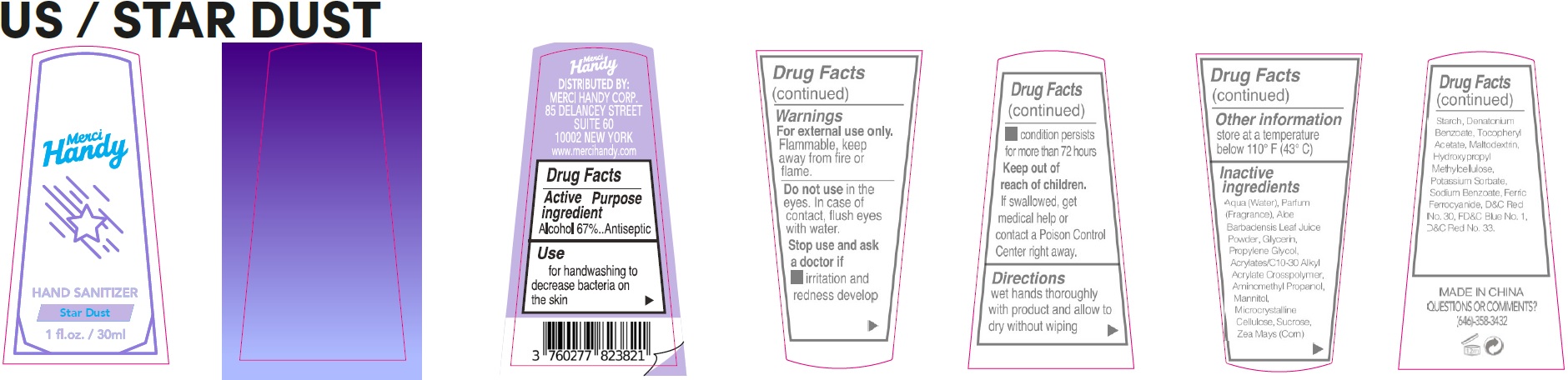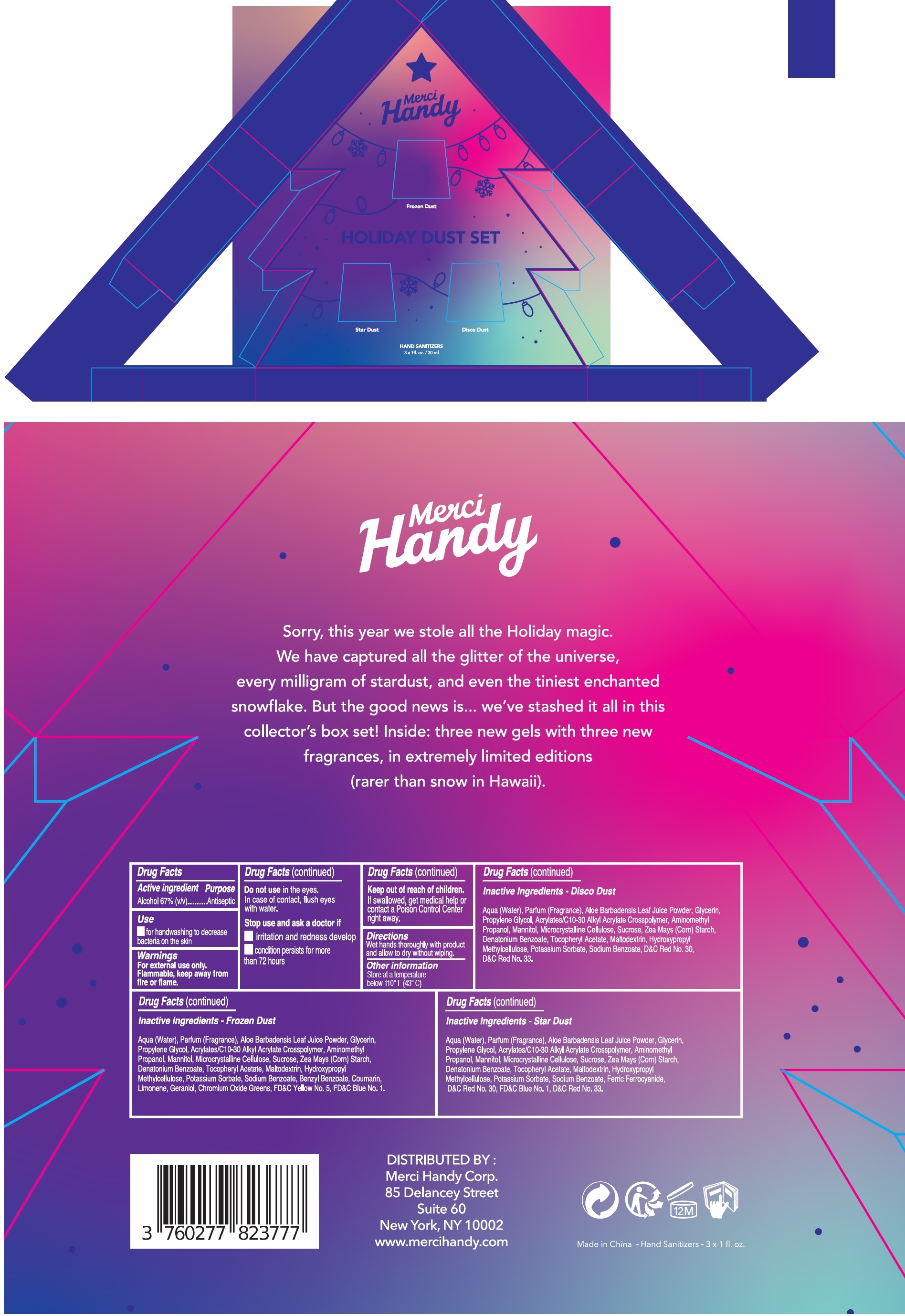 DRUG LABEL: Holiday Dust Set
NDC: 72866-030 | Form: KIT | Route: TOPICAL
Manufacturer: MERCI HANDY CORPORATION
Category: otc | Type: HUMAN OTC DRUG LABEL
Date: 20240123

ACTIVE INGREDIENTS: ALCOHOL 67 mL/100 mL; ALCOHOL 67 mL/100 mL; ALCOHOL 67 mL/100 mL
INACTIVE INGREDIENTS: WATER; ALOE VERA LEAF; GLYCERIN; PROPYLENE GLYCOL; CARBOMER INTERPOLYMER TYPE A (ALLYL SUCROSE CROSSLINKED); AMINOMETHYLPROPANOL; MANNITOL; MICROCRYSTALLINE CELLULOSE; SUCROSE; CORN; DENATONIUM BENZOATE; .ALPHA.-TOCOPHEROL ACETATE; MALTODEXTRIN; HYPROMELLOSE, UNSPECIFIED; POTASSIUM SORBATE; SODIUM BENZOATE; D&C RED NO. 30; D&C RED NO. 33; HYPROMELLOSE, UNSPECIFIED; POTASSIUM SORBATE; SODIUM BENZOATE; BENZYL BENZOATE; COUMARIN; LIMONENE, (+)-; GERANIOL; CHROMIC OXIDE; FD&C YELLOW NO. 5; FD&C BLUE NO. 1; WATER; ALOE VERA LEAF; GLYCERIN; PROPYLENE GLYCOL; CARBOMER INTERPOLYMER TYPE A (ALLYL SUCROSE CROSSLINKED); AMINOMETHYLPROPANOL; MANNITOL; MICROCRYSTALLINE CELLULOSE; SUCROSE; CORN; DENATONIUM BENZOATE; .ALPHA.-TOCOPHEROL ACETATE; MALTODEXTRIN; WATER; ALOE VERA LEAF; GLYCERIN; PROPYLENE GLYCOL; CARBOMER INTERPOLYMER TYPE A (ALLYL SUCROSE CROSSLINKED); AMINOMETHYLPROPANOL; MANNITOL; MICROCRYSTALLINE CELLULOSE; SUCROSE; CORN; DENATONIUM BENZOATE; .ALPHA.-TOCOPHEROL ACETATE; MALTODEXTRIN; HYPROMELLOSE, UNSPECIFIED; POTASSIUM SORBATE; SODIUM BENZOATE; FERRIC FERROCYANIDE; D&C RED NO. 30; FD&C BLUE NO. 1; D&C RED NO. 33

Holiday Dust Set

Active ingredient

Alcohol 67%

Purpose

Antiseptic

Use

- for handwashing to decrease bacteria on the skin

Warnings

For external use only. Flammable, keep away from fire or flame.

Do not use

in the eyes. In case of contact, flush eyes with water.

Stop use and ask a doctor if

- irritation and redness develop
- condition persists for more than 72 hours

Keep out of reach of children.

If swallowed, get medical help or contact a Poison Control Center right away.

Directions

Wet hands thoroughly with product and allow to dry without wiping

Other information

Store at a temperature below 110° F (43° C)

Inactive ingredients

Aqua (Water), Parfum (Fragrance), Aloe Barbadensis Leaf Juice Powder, Glycerin, Propylene Glycol, Acrylates/C10-30 Alkyl Acrylate Crosspolymer, Aminomethyl Propanol, Mannitol, Microcrystalline Cellulose, Sucrose, Zea Mays (Corn) Starch, Denatonium Benzoate, Tocopheryl Acetate, Maltodextrin, Hydroxypropyl Methylcellulose, Potassium Sorbate, Sodium Benzoate, D&C Red No. 30, D&C Red No. 33.

QUESTIONS OR COMMENTS?

(646)-358-3432

Active ingredient

Alcohol 67%

Purpose

Antiseptic

Use

- for handwashing to decrease bacteria on the skin

Warnings

For external use only. Flammable, keep away from fire or flame.

Do not use

in the eyes. In case of contact, flush eyes with water.

Stop use and ask a doctor if

- irritation and redness develop
- condition persists for more than 72 hours

Keep out of reach of children.

If swallowed, get medical help or contact a Poison Control Center right away.

Directions

Wet hands thoroughly with product and allow to dry without wiping

Other information

Store at a temperature below 110° F (43° C)

Inactive ingredients

Aqua (Water), Parfum (Fragrance), Aloe Barbadensis Leaf Juice Powder, Glycerin, Propylene Glycol, Acrylates/C10-30 Alkyl Acrylate Crosspolymer, Aminomethyl Propanol, Mannitol, Microcrystalline Cellulose, Sucrose, Zea Mays (Corn) Starch, Denatonium Benzoate, Tocopheryl Acetate, Maltodextrin, Hydroxypropyl Methylcellulose, Potassium Sorbate, Sodium Benzoate, Benzyl Benzoate, Coumarin, Limonene, Geraniol, Chromium Oxide Greens, FD&C Yellow No. 5, FD&C Blue No. 1.

QUESTIONS OR COMMENTS?

(646)-358-3432

Active ingredient

Alcohol 67%

Purpose

Antiseptic

Use

- for handwashing to decrease bacteria on the skin

Warnings

For external use only. Flammable, keep away from fire or flame.

Do not use

in the eyes. In case of contact, flush eyes with water.

Stop use and ask a doctor if

- irritation and redness develop
- condition persists for more than 72 hours

Keep out of reach of children.

If swallowed, get medical help or contact a Poison Control Center right away.

Directions

Wet hands thoroughly with product and allow to dry without wiping

Other information

Store at a temperature below 110° F (43° C)

Inactive ingredients

Aqua (Water), Parfum (Fragrance), Aloe Barbadensis Leaf Juice Powder, Glycerin, Propylene Glycol, Acrylates/C10-30 Alkyl Acrylate Crosspolymer, Aminomethyl Propanol, Mannitol, Microcrystalline Cellulose, Sucrose, Zea Mays (Corn) Starch, Denatonium Benzoate, Tocopheryl Acetate, Maltodextrin, Hydroxypropyl Methylcellulose, Potassium Sorbate, Sodium Benzoate, Ferric Ferrocyanide, D&C Red No. 30, FD&C Blue No. 1, D&C Red No. 33.

QUESTIONS OR COMMENTS?

(646)-358-3432